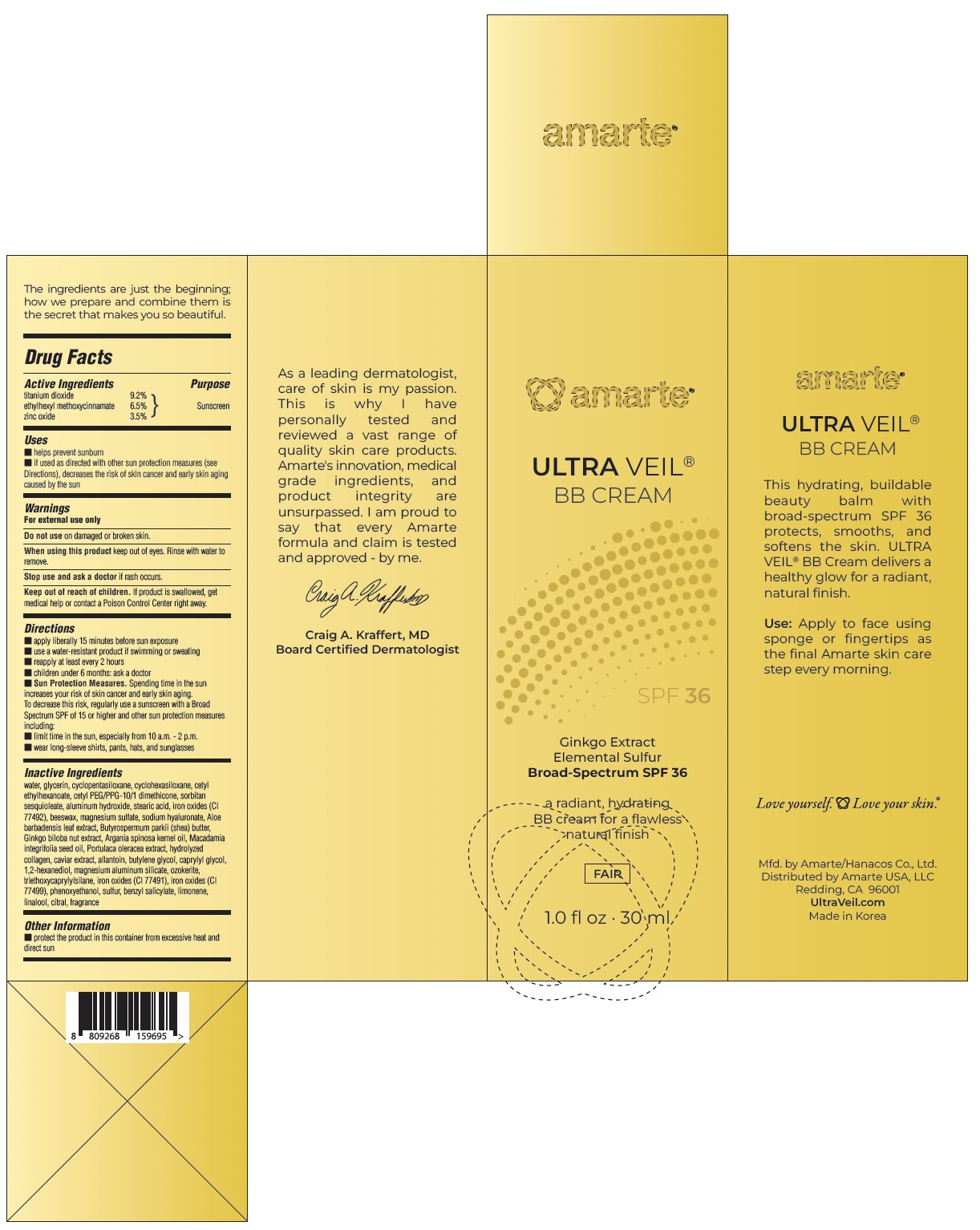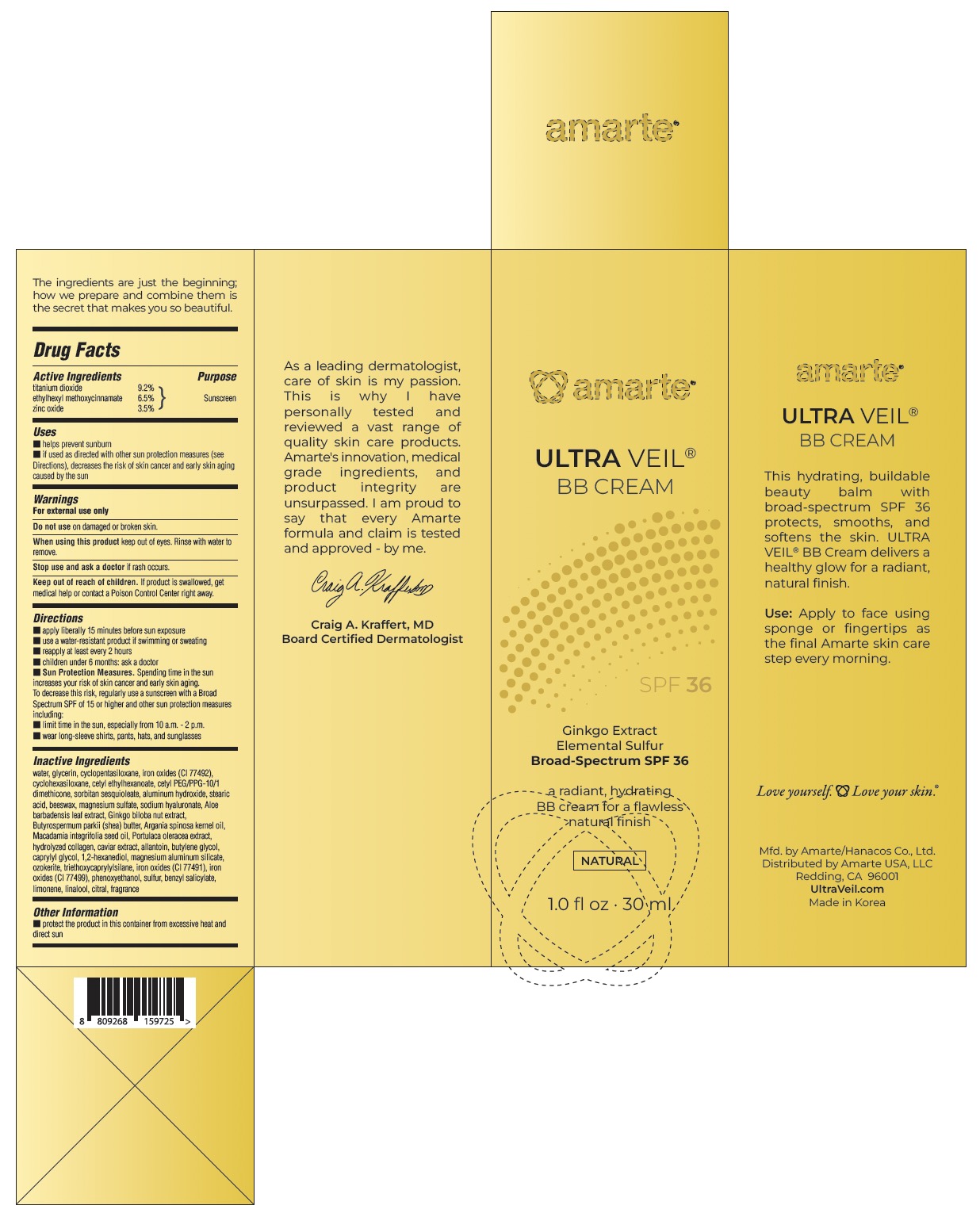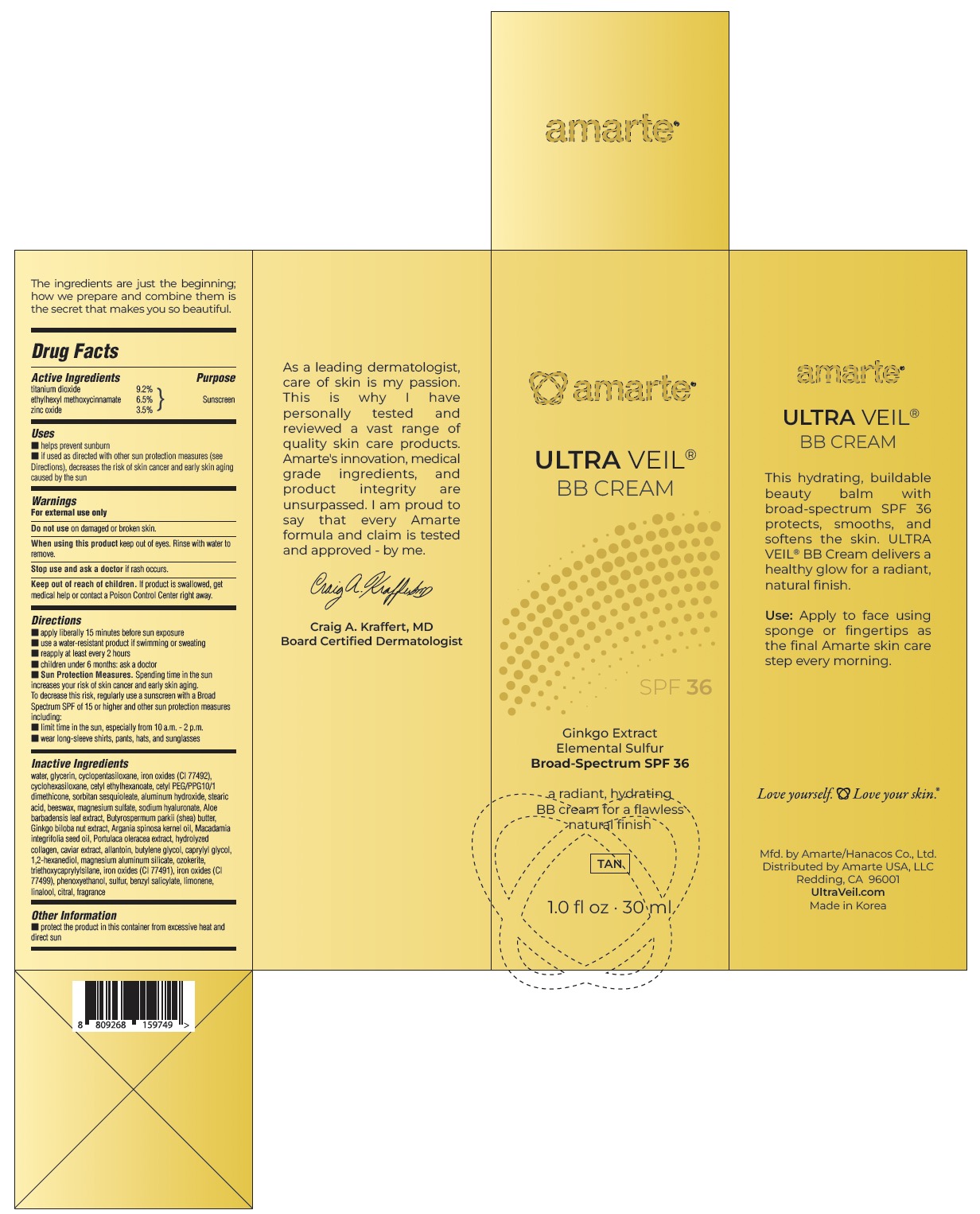 DRUG LABEL: Amarte ULTRA VEIL BB Fair
NDC: 84779-112 | Form: LOTION
Manufacturer: Amarte USA LLC
Category: otc | Type: HUMAN OTC DRUG LABEL
Date: 20250715

ACTIVE INGREDIENTS: TITANIUM DIOXIDE 92 mg/1 mL; ZINC OXIDE 35 mg/1 mL; ETHYLHEXYL METHOXYCINNAMATE 65 mg/1 mL
INACTIVE INGREDIENTS: SHEA BUTTER; CETYL ETHYLHEXANOATE; COLLAGEN ALPHA-1(I) CHAIN BOVINE; ARGAN OIL; LIMONENE, (+)-; BENZYL SALICYLATE; MACADAMIA INTEGRIFOLIA SEED OIL; ALOE VERA LEAF; CETYL PEG/PPG-10/1 DIMETHICONE (HLB 2); HYALURONATE SODIUM; GINKGO BILOBA SEED; ALUMINUM HYDROXIDE; BEESWAX; CERESIN; TRIETHOXYCAPRYLYLSILANE; SULFUR; WATER; CYCLOMETHICONE 5; ALLANTOIN; BUTYLENE GLYCOL; CYCLOMETHICONE 6; SORBITAN SESQUIOLEATE; MAGNESIUM SULFATE; GLYCERIN; FERRIC OXIDE RED; CAVIAR, UNSPECIFIED; MAGNESIUM ALUMINUM SILICATE; CAPRYLYL GLYCOL; 1,2-HEXANEDIOL; STEARIC ACID; PHENOXYETHANOL; LINALOOL; CITRAL

Amarte-Hanacos Sunscreen 3 Shades

Active Ingredient(s)

Titanium dioxide 9.2%

Ettlythexyl methoxycinnamate 6.5%

Zinc oxide 3.5%

Purpose

Sunscreen

Use

■ helps prevent sunburn ■ if used as directed with other sun protection measures (see Directions), decreases the risk of skin cancer and early skin aging caused by the sun

Warnings

For external use only
Do not use on damaged or broken skin.
When using this product keep out of eyes. Rinse with water to remove.
Stop use and ask a doctor if rash occurs.
Keep out of reach of children. If product is swallowed, get medical help or contact a Poison Control Center right away.

WHEN USING

keep out of eyes. Rinse with water to remove.

KEEP OUT OF REACH OF CHILDREN

If product is swallowed, get medical help or contact a Poison Control Center right away.

Directions

Directions ■ shake well ■ apply liberally 15 minutes before sun exposure ■ use a water-resistant product if swimming or sweating ■ reapply at least every 2 hours ■ children under 6 months: ask a doctor ■ Sun Protection Measures. Spending time in the sun increases your risk of skin cancer and early skin aging. To decrease this risk, regularly use a sunscreen with a Broad Spectrum SPF of 15 or higher and other sun protection measures including: ■ limit time in the sun, especially from 10 a.m. - 2 p.m. ■ wear long-sleeve shirts, pants, hats, and sunglasses

Inactive ingredients

water, glycerin, cyclopentasiloxane, cyclohexasiloxane, cetyl ethylhexanoate, cetyl peg/ppg-10/1 dimethicone, sorbitan sesquioleate, aluminum hydroxide, stearic acid, iron oxides (ci 77492), beeswax, magnesium sulfate, sodium hyaluronate, aloe barbadensis leaf extract, butyrospermum parkii (shea) butter, ginkgo biloba nut extract, argania spinosa kernel oil, macadamia integrifolia seed oil, portulaca oleracea extract, hydrolyzed collagen, caviar extract, allantoin, butylene glycol, caprylyl glycol, 1,2-hexanediol, magnesium aluminum silicate, ozokerite, triethoxycaprylylsilane, iron oxides (ci 77491), iron oxides (ci 77499), phenoxyethanol, sulfur, benzyl salicylate, limonene, citral, fragrance

Other information

■ protect the product in this container from excessive heat and direct sun